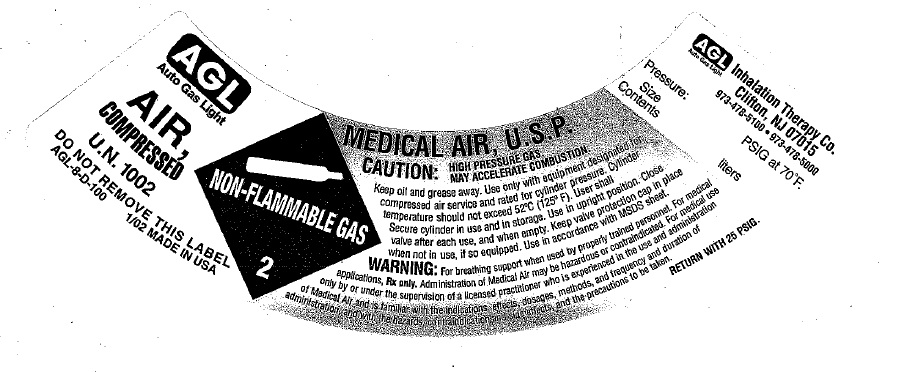 DRUG LABEL: Air
NDC: 17575-007 | Form: GAS
Manufacturer: AGL Inhalation Therapy Co.
Category: prescription | Type: HUMAN PRESCRIPTION DRUG LABEL
Date: 20100429

ACTIVE INGREDIENTS: Air 1000 mL/1 L

air

PACKAGE LABEL

AGL
Auto Gas Light
AIR,
COMPRESSED
U.N. 1002
DO NOT REMOVE THIS LABEL
AGL-8-D-100 1/02 MADE IN USA
NON-FLAMMABLE GAS 2
MEDICAL AIR, U.S.P.
CAUTION: HIGH PRESSURE GAS. MAY ACCELERATE COMBUSTION.
Keep oil and grease away. Use only with equipment designated for compressed air service and rated for cylinder pressure. Cylinder temperature should not exceed 52 degrees C (125 degrees F). User shall Secure cylinder in use and in storage. Use in upright position. Close valve after each use, and when empty. Keep valve protection cap in place when not in use, if so equipped. Use in accordance with MSDS sheet.
WARNING: For breathing support when used by properly trained personnel. For medical applications, RX only. Administration of Medical Air may be hazardous or contraindicated. For medical use only by or under the supervision of a licensed practitioner who is experienced in the use and administration of Medical Air and is familiar with the indications, effects, dosages, methods, and frequency and duration of administration and with the hazards, contraindication and side effects and the precautions to be taken.
RETURN WITH 25 PSIG.
AGL Inhalation Therapy Co. Clifton, NJ 07015
973-478-5100
973-478-5000
Pressure: PSIG at 70 degrees F.
Size
Contents liters